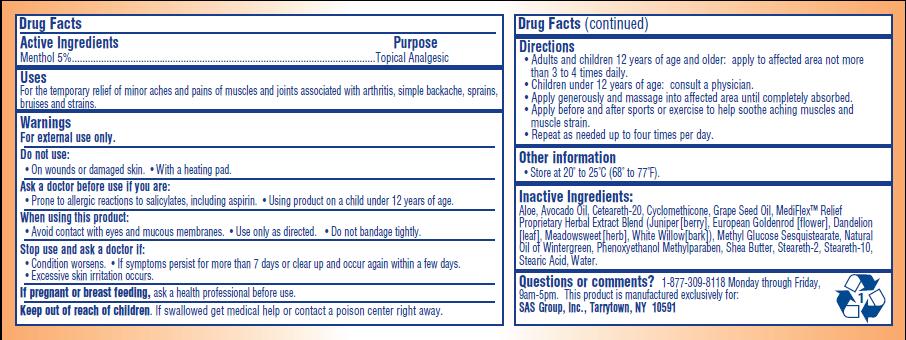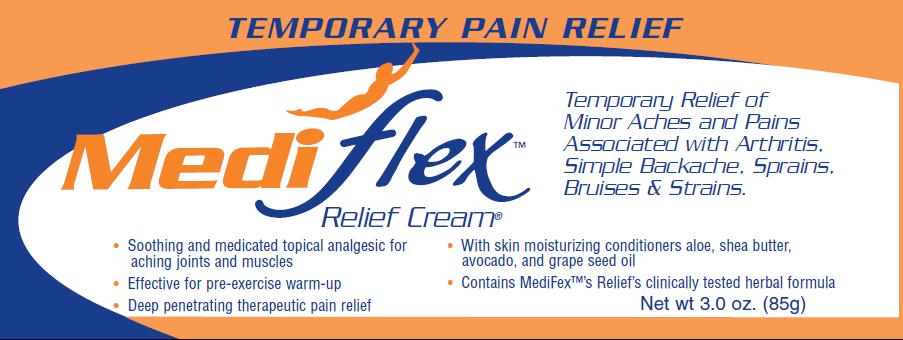 DRUG LABEL: Mediflex
NDC: 67662-001 | Form: CREAM
Manufacturer: SAS Group Inc.
Category: otc | Type: HUMAN OTC DRUG LABEL
Date: 20100407

ACTIVE INGREDIENTS: MENTHOL 5 1/85 g

ACTIVE INGREDIENT

Menthol 5%

PURPOSE

Topical Analgesic

INDICATIONS AND USAGE

For the temporary relief of minor aches and pains of muscles and joints associated with arthritis, simple backache, sprains, bruises and strains.

WARNINGS

For external use only.

Do not use:

- on wounds or damaged skin
- with a heading pad

Ask a doctor before use if you are:

- prone to allergic reactions to salicylates, including aspirin
- using a product on a child under 12 years of age

When using this product:

- avoid contact with eyes and mucous membranes
- use only as directed
- do not bandage tightly

Stop use and ask a doctor if:

- Condition worsens
- If symptoms persist for more than 7 days or clear up and occur within a few days
- Excessive skin irritation occurs

PREGNANCY OR BREAST FEEDING

If pregnant or breast feeding, ask a health professional before use.

Keep out of reach of children. If swallowed get medical help or contact a poison control center right away.

Directions:

- Adults and children 12 years of age and older: apply to affected area not more than 3 to 4 times daily
- Children under 12 years of age: consult a physician
- Apply generously and massage into affected area until completely absorbed
- Apply before and after sports or exercise to help soothe aching muscles and muscle strain
- Repeat as needed up to four times per day

STORAGE AND HANDLING

Store at 20 to 25 degrees Celsius (68 to 77 degrees F)

INACTIVE INGREDIENT

Aloe, Avocado Oil, Ceteareth-20, Cylcomethicone, Grape Seed Oil, MediFlex Relief Proprietary Herbal Extract Blend (juniper [berry], European Goldenrod [flower], Dandelion [leaf], Meadowsweet [herb], White Willow [bark], Methyl Glucose Sesquisterate, Natural Oil of Wintergreen, Phenoxyethanol Methylparaben, Shea Butter, Steareth-2, Stearath-10, Stearic Acid, Water

Questions or comments? 1-877-309-8118 Monday through Friday, 9am-5pm.

DESCRIPTION

This product is manufactured exclusively for: SAS Group, Inc., Tarrytown, NY 10591

PACKAGE LABEL

Temporary Pain Relief

Mediflex Relief Cream

Temporary Relief of Minor Aches and Pains Associated with Arthritis, Simple Backache, Sprains, Bruises and Strains.

- Soothing and medicated topical analgesic for aching joints and muscles
- Effective for pre-exercise warm-up
- Deep penetrating therapeutic pain relief
- With skin moisturizing conditions aloe, shea butter, avocado, and grape seed oil
- Contains MediFlex Relief's clinically tested herbal formula